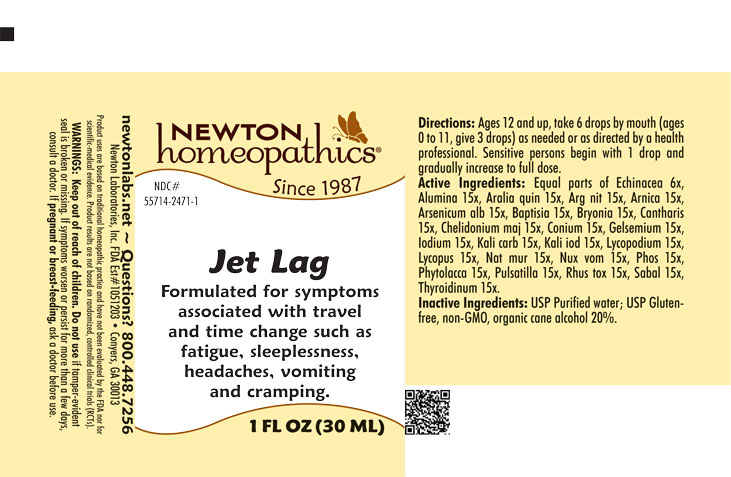 DRUG LABEL: Jet Lag
NDC: 55714-2471 | Form: LIQUID
Manufacturer: Newton Laboratories, Inc.
Category: homeopathic | Type: HUMAN OTC DRUG LABEL
Date: 20250918

ACTIVE INGREDIENTS: ECHINACEA, UNSPECIFIED 6 [hp_X]/1 mL; AMERICAN GINSENG 15 [hp_X]/1 mL; SILVER NITRATE 15 [hp_X]/1 mL; ARNICA MONTANA 15 [hp_X]/1 mL; ARSENIC TRIOXIDE 15 [hp_X]/1 mL; BAPTISIA TINCTORIA ROOT 15 [hp_X]/1 mL; BRYONIA ALBA ROOT 15 [hp_X]/1 mL; LYTTA VESICATORIA 15 [hp_X]/1 mL; CHELIDONIUM MAJUS 15 [hp_X]/1 mL; CONIUM MACULATUM FLOWERING TOP 15 [hp_X]/1 mL; GELSEMIUM SEMPERVIRENS ROOT 15 [hp_X]/1 mL; IODINE 15 [hp_X]/1 mL; POTASSIUM CARBONATE 15 [hp_X]/1 mL; POTASSIUM IODIDE 15 [hp_X]/1 mL; LYCOPODIUM CLAVATUM SPORE 15 [hp_X]/1 mL; LYCOPUS VIRGINICUS 15 [hp_X]/1 mL; SODIUM CHLORIDE 15 [hp_X]/1 mL; STRYCHNOS NUX-VOMICA SEED 15 [hp_X]/1 mL; PHOSPHORUS 15 [hp_X]/1 mL; PHYTOLACCA AMERICANA ROOT 15 [hp_X]/1 mL; ANEMONE PULSATILLA 15 [hp_X]/1 mL; TOXICODENDRON PUBESCENS LEAF 15 [hp_X]/1 mL; SAW PALMETTO 15 [hp_X]/1 mL; ALUMINUM OXIDE 15 [hp_X]/1 mL; THYROID, UNSPECIFIED 15 [hp_X]/1 mL
INACTIVE INGREDIENTS: ALCOHOL; WATER

Jet 2471L

INDICATIONS & USAGE SECTION

Formulated for symptoms associated with travel and time change such as fatigue, sleeplessness, headaches, vomiting and cramping.

DOSAGE & ADMINISTRATION SECTION

Directions: Ages 12 and up, take 6 drops by mouth (ages 0 to 11, give 3 drops) as needed or as directed by a health professional. Sensitive persons begin with 1 drop and gradually increase to full dose.

OTC - ACTIVE INGREDIENT SECTION

Equal parts of Echinacea 6x, Alumina 15x, Aralia quinquefolia 15x, Argentum nitricum 15x, Arnica montana 15x, Arsenicum album 15x, Baptisia tinctoria 15x, Bryonia 15x, Cantharis 15x, Chelidonium majus 15x, Conium maculatum 15x, Gelsemium sempervirens 15x, Iodium 15x, Kali carbonicum 15x, Kali iodatum 15x, Lycopodium clavatum 15x, Lycopus virginicus 15x, Natrum muriaticum 15x, Nux vomica 15x, Phosphorus 15x, Phytolacca decandra 15x, Pulsatilla 15x, Rhus toxicodendron 15x, Sabal serrulata 15x, Thyroidinum 15x.

OTC - PURPOSE SECTION

Formulated for symptoms associated with travel and time change such as fatigue, sleeplessness, headaches, vomiting and cramping.

INACTIVE INGREDIENT SECTION

Inactive Ingredients: USP Purified Water; USP Gluten-free, non-GMO, organic cane alcohol 20%.

QUESTIONS SECTION

newtonlabs.net – Questions? 800.448.7256

Newton Laboratories, Inc. FDA Est # 1051203 - Conyers, GA 30013

WARNINGS SECTION

WARNINGS: Keep out of reach of children. Do not use if tamper-evident seal is broken or missing. If symptoms worsen or persist for more than a few days, consult a doctor. If pregnant or breast-feeding, ask a doctor before use.

OTC - PREGNANCY OR BREAST FEEDING SECTION

If pregnant or breast-feeding, ask a doctor before use.

OTC - KEEP OUT OF REACH OF CHILDREN SECTION

Keep out of reach of children.